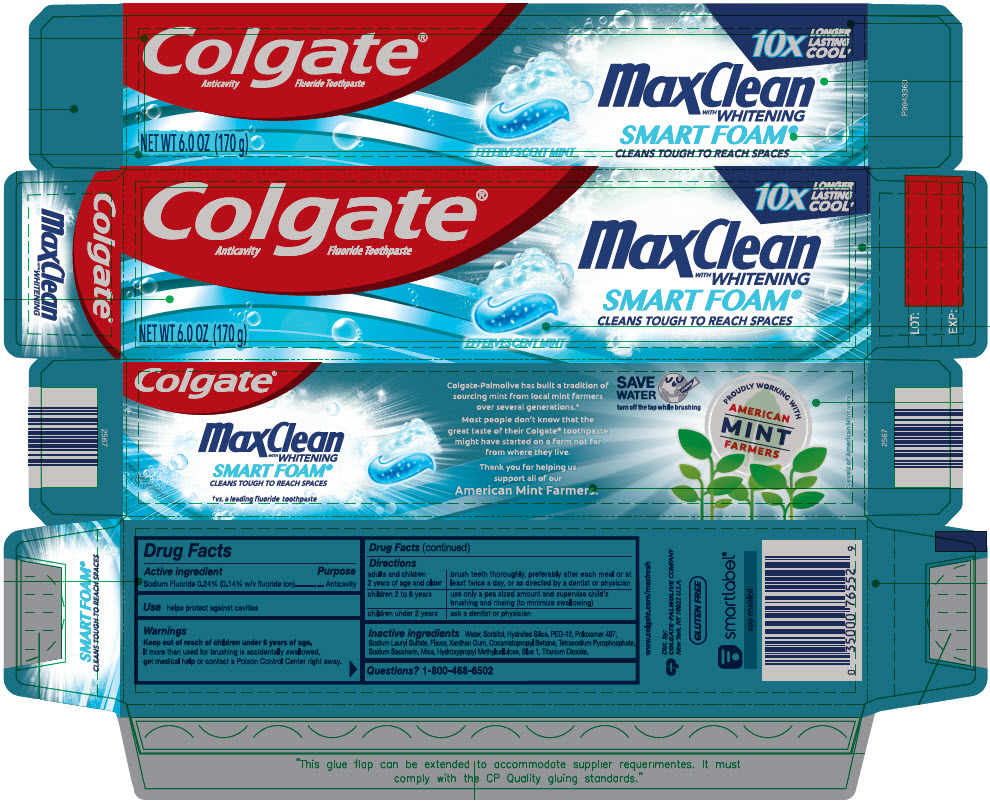 DRUG LABEL: Colgate MaxClean with Whitening Smartfoam
NDC: 35000-028 | Form: PASTE, DENTIFRICE
Manufacturer: Colgate-Palmolive Company
Category: otc | Type: HUMAN OTC DRUG LABEL
Date: 20250501

ACTIVE INGREDIENTS: SODIUM FLUORIDE 1.1 mg/1 g
INACTIVE INGREDIENTS: SORBITOL; WATER; HYDRATED SILICA; POLYETHYLENE GLYCOL 600; POLOXAMER 407; SODIUM LAURYL SULFATE; XANTHAN GUM; COCAMIDOPROPYL BETAINE; SODIUM PYROPHOSPHATE; SACCHARIN SODIUM; MICA; HYPROMELLOSE, UNSPECIFIED; FD&C BLUE NO. 1; TITANIUM DIOXIDE

Colgate® MaxClean™ with Whitening Smartfoam®

Drug Facts

Active ingredient

Sodium Fluoride 0.24% (0.14% w/v fluoride ion)

Purpose

Anticavity

Use

helps protect against cavities

Warnings

Keep out of reach of children under 6 years of age.

If more than used for brushing is accidentally swallowed, get medical help or contact a Poison Control Center right away.

Directions

adults and children 2 years of age and older | brush teeth thoroughly, preferably after each meal or at least twice a day, or as directed by a dentist or physician
children 2 to 6 years | use only a pea sized amount and supervise child's brushing and rinsing (to minimize swallowing)
children under 2 years | ask a dentist or physician

Inactive ingredients

Water, Sorbitol, Hydrated Silica, PEG-12, Poloxamer 407, Sodium Lauryl Sulfate, Flavor, Xanthan Gum, Cocamidopropyl Betaine, Tetrasodium Pyrophosphate Sodium Saccharin, Mica, Hydroxypropyl Methylcellulose, Blue 1, Titanium Dioxide.

Questions?

1-800-468-6502

Dist. by:
COLGATE-PALMOLIVE CO.
New York, NY 10022 U.S.A.

PRINCIPAL DISPLAY PANEL - 170 g Tube Carton

Colgate®
Anticavity Fluoride Toothpaste

10x
LONGER
LASTING
COOL†

MaxClean
with WHITENING

SMART FOAM®
CLEANS TOUGH TO REACH SPACES

NET WT 6.0 OZ (170 g)

EFFERVESCENT MINT